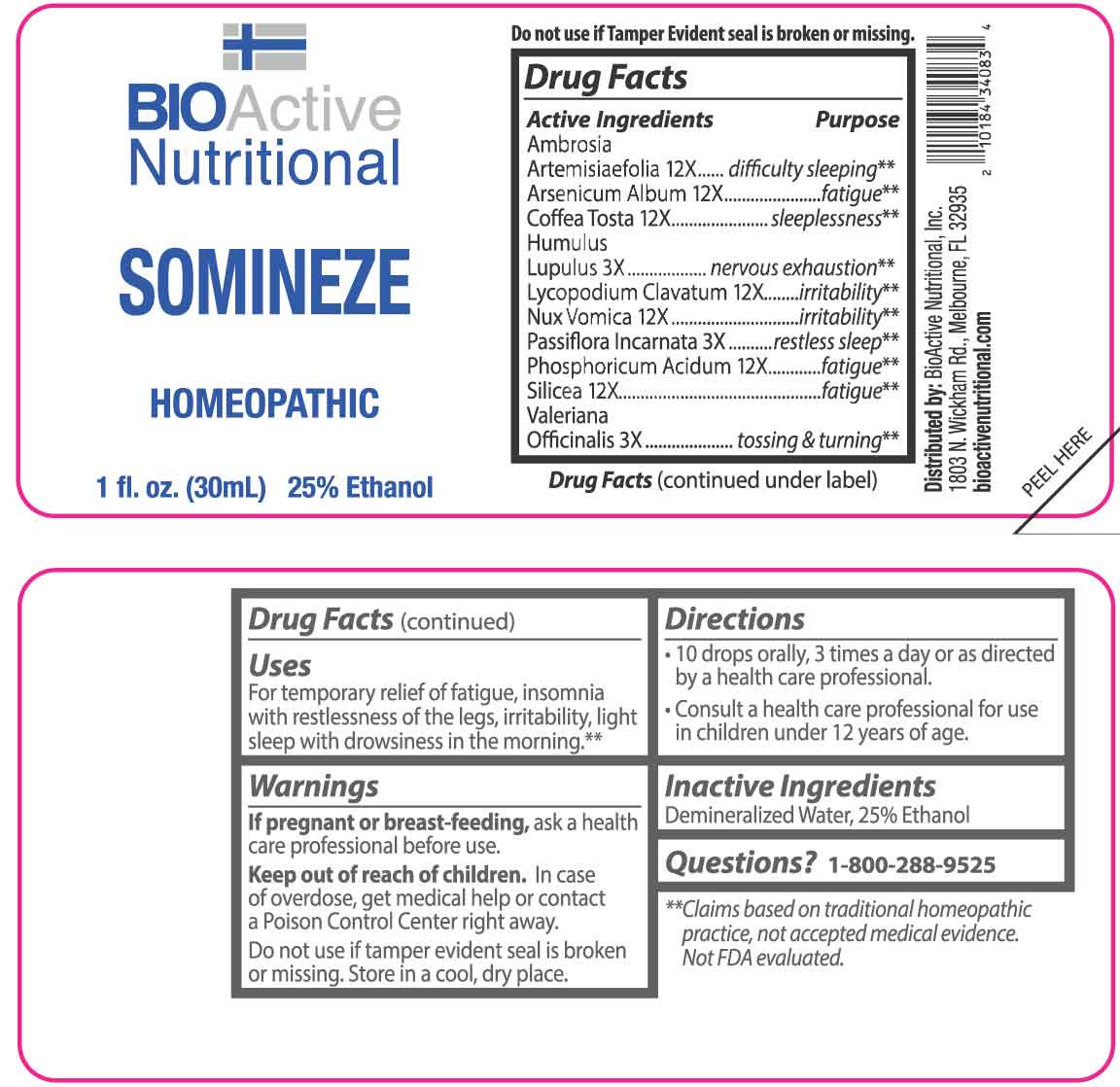 DRUG LABEL: Somineze
NDC: 43857-0379 | Form: LIQUID
Manufacturer: BioActive Nutritional, Inc.
Category: homeopathic | Type: HUMAN OTC DRUG LABEL
Date: 20251218

ACTIVE INGREDIENTS: HOPS 3 [hp_X]/1 mL; PASSIFLORA INCARNATA FLOWERING TOP 3 [hp_X]/1 mL; VALERIAN 3 [hp_X]/1 mL; AMBROSIA ARTEMISIIFOLIA WHOLE 12 [hp_X]/1 mL; ARSENIC TRIOXIDE 12 [hp_X]/1 mL; COFFEA ARABICA SEED, ROASTED 12 [hp_X]/1 mL; LYCOPODIUM CLAVATUM SPORE 12 [hp_X]/1 mL; STRYCHNOS NUX-VOMICA SEED 12 [hp_X]/1 mL; PHOSPHORIC ACID 12 [hp_X]/1 mL; SILICON DIOXIDE 12 [hp_X]/1 mL
INACTIVE INGREDIENTS: WATER; ALCOHOL

DRUG FACTS:

ACTIVE INGREDIENTS:

Ambrosia Artemisiaefolia 12X, Arsenicum Album 12X, Coffea Tosta 12X, Humulus Lupulus 3X, Lycopodium Clavatum 12X, Nux Vomica 12X, Passiflora Incarnata 3X, Phosphoricum Acidum 12X, Silicea 12X, Valeriana Officinalis 3X.

PURPOSE:

Ambrosia Artemisiaefolia – difficulty sleeping,** Arsenicum Album - fatigue,** Coffea Tosta - sleeplessness,** Humulus Lupulus – nervous exhaustion,** Lycopodium Clavatum - irritability,** Nux Vomica - irritability,** Passiflora Incarnata – restless sleep,** Phosphoricum Acidum – fatigue,** Silicea - fatigue,** Valeriana Officinalis – tossing & turning**

**Claims based on traditional homeopathic practice, not accepted medical evidence. Not FDA evaluated.

USES:

For temporary relief of fatigue, insomnia with restlessness of the legs, irritability, light sleep with drowsiness in the morning.**

**Claims based on traditional homeopathic practice, not accepted medical evidence. Not FDA evaluated.

WARNINGS:

If pregnant or breast-feeding, ask a health care professional before use.

Keep out of reach of children. In case of overdose, get medical help or contact a Poison Control Center right away.

Do not use if tamper evident seal is broken or missing.

Store in a cool, dry place.

KEEP OUT OF REACH OF CHILDREN:

In case of overdose, get medical help or contact a Poison Control Center right away.

DIRECTIONS:

• 10 drops orally, 3 times a day or as directed by a health care professional.

• Consult a health care professional for use in children under 12 years of age.

INACTIVE INGREDIENTS:

Demineralized Water, 25% Ethanol

QUESTIONS:

Distributed by:

BioActive Nutritional, Inc.

1803 N. Wickham Rd.

Melbourne, FL 32935

bioactivenutritional.com

1-800-288-9525

PACKAGE LABEL DISPLAY:

BIOActive Nutritional

SOMINEZE

HOMEOPATHIC

1 fl. oz. (30 mL)